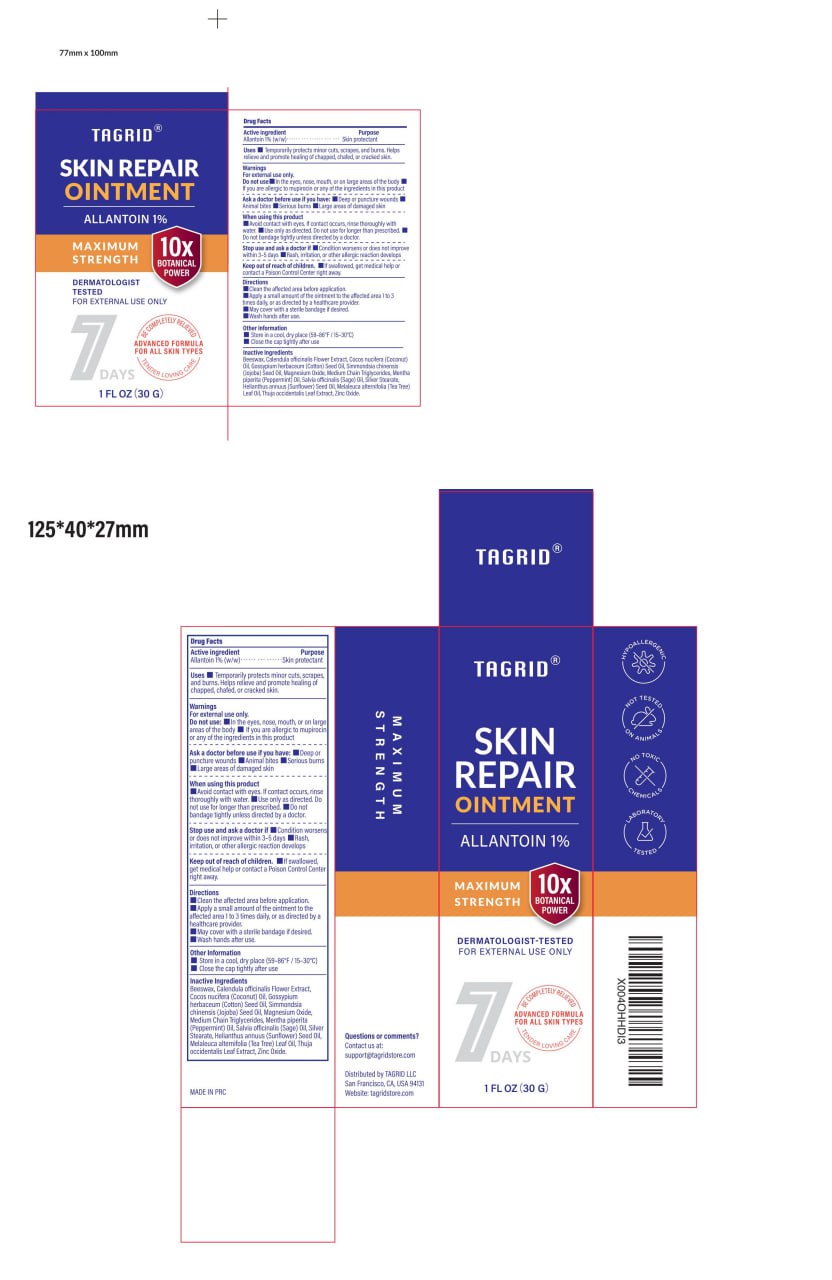 DRUG LABEL: Tagrid Skin Repair Cream
NDC: 85384-0007 | Form: CREAM
Manufacturer: TAGRID LLC
Category: otc | Type: HUMAN OTC DRUG LABEL
Date: 20250508

ACTIVE INGREDIENTS: ALLANTOIN 10 mg/1 g
INACTIVE INGREDIENTS: GOSSYPIUM HERBACEUM (COTTON) SEED OIL; MENTHA PIPERITA (PEPPERMINT) OIL; SALVIA OFFICINALIS (SAGE) OIL; SILVER STEARATE; ZINC OXIDE; CALENDULA OFFICINALIS FLOWER; SIMMONDSIA CHINENSIS (JOJOBA) SEED OIL; THUJA OCCIDENTALIS LEAF; COCOS NUCIFERA (COCONUT) OIL; BEESWAX; MAGNESIUM OXIDE; MELALEUCA ALTERNIFOLIA (TEA TREE) LEAF OIL; MEDIUM-CHAIN TRIGLYCERIDES; SUNFLOWER OIL

Initial Drug Listing-Tagrid Skin Repair Ointment Allantoin 1%

ACTIVE INGREDIENT

Allantoin 1% (w/w/)

PURPOSE

Skin protectant

INDICATIONS AND USAGE

Temporarily protects minor cuts, scrapes, and burns. Helps relieve and promote healing of chapped, chafed, or cracked skin.

WARNINGS

For external use only

Do not use: In the eyes, nose, mouth, or on large
areas of the body
If you are allergic to mupirocin or any of the ingredients in this product

Ask a doctor before use if you have:
Deep or puncture wounds
Animal bites

Serious burns
Large areas of damaged skin

WHEN USING

■ Avoid contact with eyes. If contact occurs, rinse thoroughly with water.
■ Use only as directed. Do not use for longer than prescribed.
■ Do not bandage tightly unless directed by a doctor.

Stop use and ask a doctor if

Condition worsens or does not improve within 3-5 days
Rash,irritation, or other allergic reaction develops

KEEP OUT OF REACH OF CHILDREN

If swallowed, get medical help or contact a Poison Control Center right away.

Directions
Clean the affected area before application.
Apply a small amount of the ointment to the affected area 1 to 3 times daily, or as directed by a
healthcare provider.
May cover with a sterile bandage if desired.
Wash hands after use.

OTHER SAFETY INFORMATION

Store in a cool, dry place (59-86°F/15-30°C)
Close the cap tightly after use

Questions or comments?
Contact us at:
support@tagridstore.com

Distributed by TAGRID LLC
San Francisco, CA, USA 94131
Website: tagridstore.com

INACTIVE INGREDIENT

Beeswax,

Calendula officinalis Flower Extract,
Cocos nucifera (Coconut) Oil,

Gossypium herbaceum (Cotton) Seed Oil,

Simmondsia chinensis (Jojoba) Seed Oil,

Magnesium Oxide,
Medium Chain Triglycerides,

Mentha piperita
(Peppermint) Oil,

Salvia officinalis (Sage) Oil,

Silver Stearate,

Helianthus annuus (Sunflower) Seed Oil,
Melaleuca alternifolia (Tea Tree) Leaf Oil,

Thuja occidentalis Leaf Extract,

Zinc Oxide.

PACKAGE LABEL

Available in 30 g, 20 g and 15 g tube. All packages look the same externally, with the only variation being fill volume.